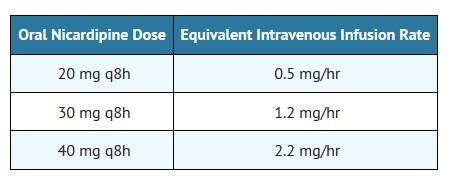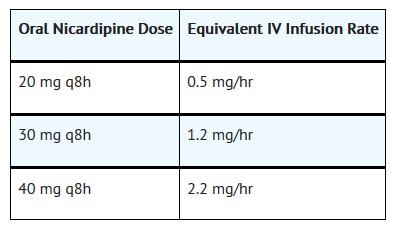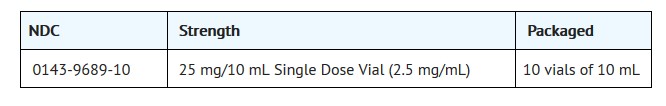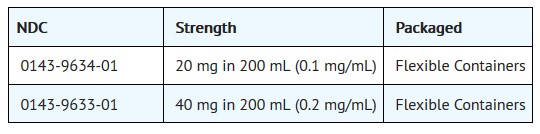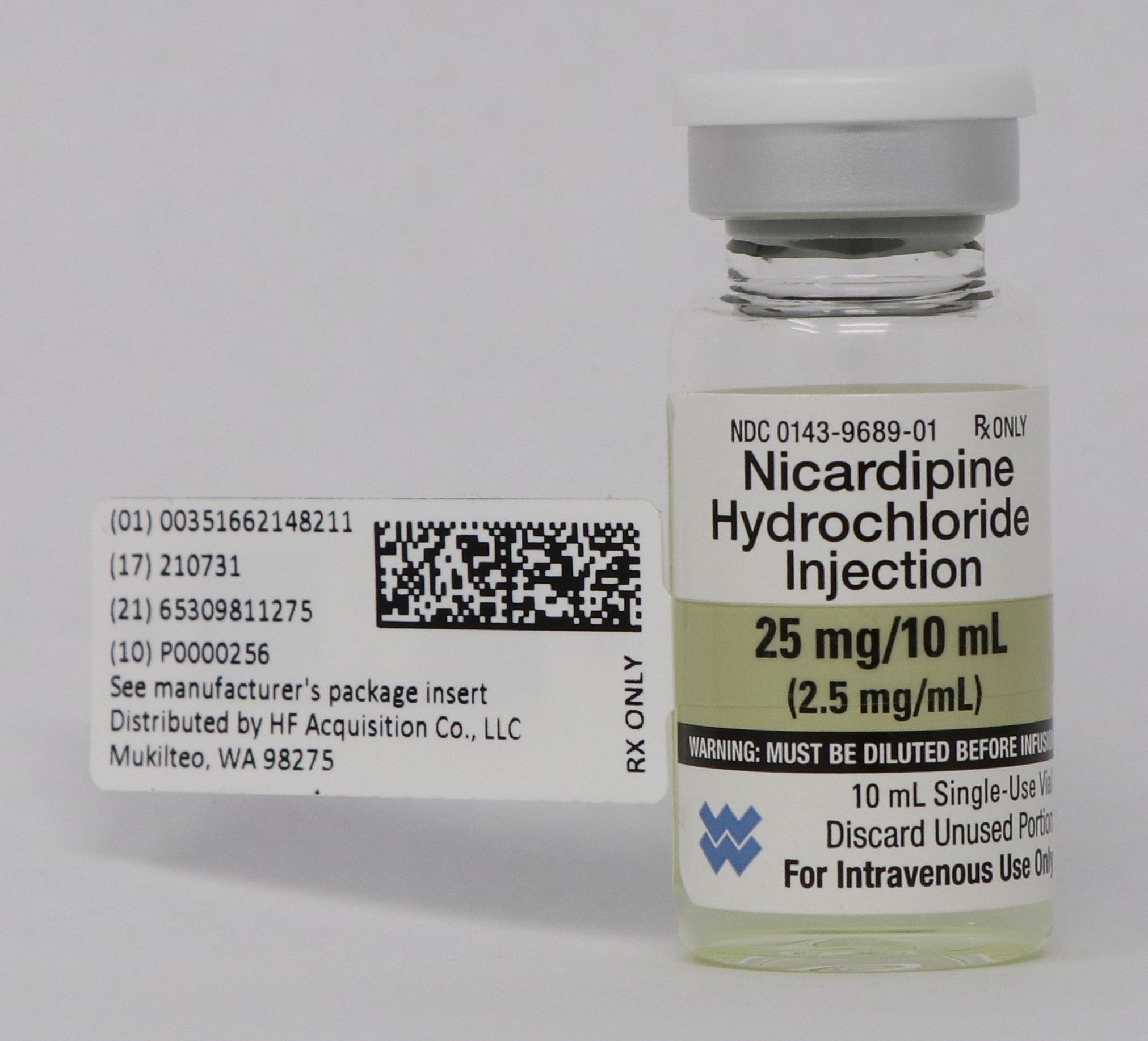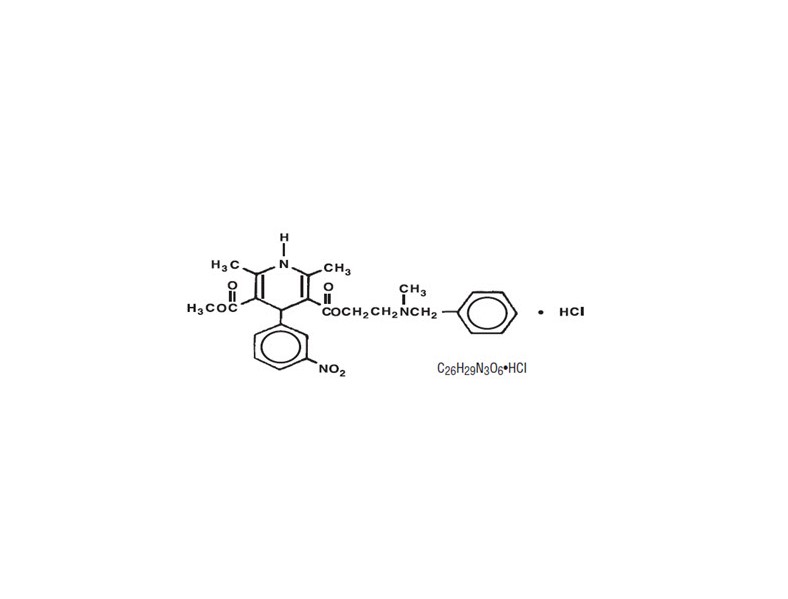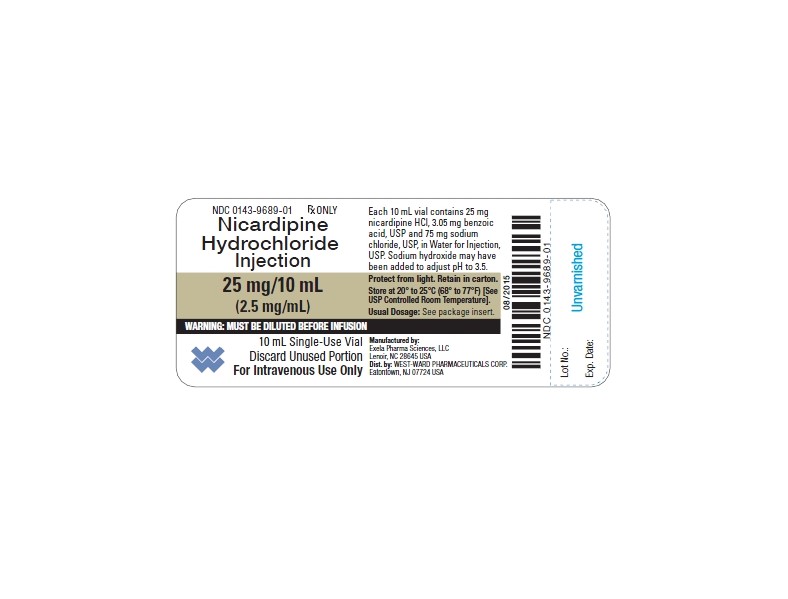 DRUG LABEL: NICARDIPINE HYDROCHLORIDE
NDC: 51662-1482 | Form: INJECTION
Manufacturer: HF Acquisition Co LLC, DBA HealthFirst
Category: prescription | Type: HUMAN PRESCRIPTION DRUG LABEL
Date: 20250108

ACTIVE INGREDIENTS: NICARDIPINE HYDROCHLORIDE 25 mg/10 mL
INACTIVE INGREDIENTS: SODIUM HYDROXIDE; 2,4-DIHYDROXYBENZOIC ACID; SODIUM CHLORIDE

NICARDIPINE HYDROCHLORIDE INJECTION 25mg/10mL (2.5 mg/mL) 10mL VIAL

HIGHLIGHTS OF PRESCRIBING INFORMATION

These highlights do not include all the information needed to use NICARDIPINE HYDROCHLORIDE safely and effectively. See full prescribing information for NICARDIPINE HYDROCHLORIDE.
NICARDIPINE HYDROCHLORIDE injection, for intravenous use
Initial U.S. Approval: 1988

RECENT MAJOR CHANGES

Dosage and Administration (2-2.2) 04/2016

INDICATIONS AND USAGE

Nicardipine hydrochloride injection is a calcium channel blocker indicated for the short-term treatment of hypertension when oral therapy is not feasible. (1)

DOSAGE AND ADMINISTRATION

Individualize dosage based upon the severity of hypertension and response of the patient during dosing (2-2.1).
Single dose vials must be diluted before use (2-2.2).
When substituting for oral nicardipine therapy, use the intravenous infusion rate as follows (2-2.3):

In a drug-free patient, initiate therapy at 5 mg/hr. Increase the infusion rate by 2.5 mg/hr to a maximum of 15 mg/hr until desired blood pressure reduction is achieved. For a gradual blood pressure reduction the rate can be increased every 15 minutes, for a rapid reduction, every 5 minutes (2-2.4).

If hypotension or tachycardia ensues, discontinue the infusion. After stabilized, patient can be restarted at low doses such as 3 to 5 mg/hr (2.5).

DOSAGE FORMS AND STRENGTHS

25 mg/10 mL (2.5 mg/mL) single-dose vial (3)
20 mg in 200 mL (0.1 mg/mL) flexible container (3)
40 mg in 200 mL (0.2 mg/mL) flexible container (3)

CONTRAINDICATIONS

Do not use in patients with advanced aortic stenosis (4-4.1).

WARNINGS AND PRECAUTIONS

To reduce the possibility of venous thrombosis, phlebitis, and vascular impairment, do not use small veins, such as those on the dorsum of the hand or wrist. Avoid intraarterial administration or extravasation (5-5.7).

To minimize the risk of peripheral venous irritation, change the site of infusion of nicardipine every 12 hours (5-5.7).

Nicardipine is not a beta-blocker and therefore gives no protection against the dangers of abrupt beta-blocker withdrawal. Withdraw beta-blockers gradually (5-5.8).

Closely monitor response in patients with angina (5-5.3), congestive heart failure (5.4), impaired hepatic function (5-5.5), portal hypertension (5-5.5), and renal impairment (5-5.6) and pheochromocytoma (5-5.9).

ADVERSE REACTIONS

Most common adverse reactions are headache (13%), hypotension (5%), tachycardia (4%) and nausea/vomiting (4%). (6)

To report SUSPECTED ADVERSE REACTIONS, contact West-Ward Pharmaceuticals at 1-877-233-2001 or the FDA at 1-800-FDA-1088 or www.fda.gov/medwatch. (6)

DRUG INTERACTIONS

Cimetidine increases nicardipine plasma levels (7-7.3).

Nicardipine may increase cyclosporine and tacrolimus plasma levels. Frequent monitoring of trough blood levels of cyclosporine and tacrolimus is recommended when co-administering nicardipine. (7-7.5, 7-7.6).

USE IN SPECIFIC POPULATIONS

Pregnancy: Based on animal data, may cause fetal harm (8-8.1).

Nursing Mothers: It is recommended that women who wish to breastfeed should not be given this drug (8-8.3).

Safety and efficacy in patients under the age of 18 have not been established (8-8.4).

Revised: 9/2016

1 INDICATIONS & USAGE

1.1 Hypertension

Nicardipine hydrochloride injection is indicated for the short-term treatment of hypertension when oral therapy is not feasible or desirable. For prolonged control of blood pressure, transfer patients to oral medication as soon as their clinical condition permits [see Dosage and Administration (2.6)].

2 DOSAGE & ADMINISTRATION

2.1 General Information

Individualize dosing based on the severity of hypertension and the response of the patient during dosing. Monitor blood pressure and heart rate both during and after the infusion to avoid tachycardia or too rapid or excessive reduction in either systolic or diastolic blood pressure.

Administer Nicardipine Hydrochloride by slow continuous infusion by a central line or through a large peripheral vein. Change the infusion site every 12 hours if administered via peripheral vein [see Intravenous Infusion Site (5-5.7)].

2.2 Inspection and Preparation

Parenteral drug products should be inspected visually for particulate matter and discoloration prior to administration, whenever solution and container permit.

Do not use the solution if particulate matter, precipitate, or crystallization is present, or if the container appears damaged.

Single Dose Vials

Dilution

Single dose vials must be diluted before infusion.

Each vial (25 mg) must be diluted with 240 mL of compatible intravenous fluid (see below), resulting in 250 mL of solution at a concentration of 0.1 mg/mL.

Compatability

Nicardipine hydrochloride injection has been found compatible and stable in polyvinyl chloride containers for 24 hours at controlled room temperature with:

Dextrose (5%) Injection, USP
Dextrose (5%) and Sodium Chloride (0.45%) Injection, USP
Dextrose (5%) and Sodium Chloride (0.9%) Injection, USP
Dextrose (5%) with 40 mEq Potassium, USP
Sodium Chloride (0.45%) Injection, USP
Sodium Chloride (0.9%) Injection, USP

Nicardipine hydrochloride is not compatible with Sodium Bicarbonate (5%) Injection, USP or Lactated Ringer’s Injection, USP.

Flexible Containers

Dilution is not required for Nicardipine Hydrochloride in 0.9% Sodium Chloride Injection.

Check the container for minute leaks prior to use by squeezing the bag firmly; ensure that the seal is intact. If leaks are found, discard solution as sterility may be impaired.

Do not combine Nicardipine Hydrochloride in 0.9% Sodium Chloride Injection with any product in the same intravenous line or premixed container. Do not add supplementary medication to the bag. Protect from light until ready to use.

Do not use plastic containers in series connections. Such use could result in air embolism due to residual air being drawn from the primary container before the administration of the fluid from the secondary container is complete.

Preparation for administration

1. Suspend container from eyelet support.

2. Remove protector from outlet port at bottom of container.

3. Attach administration set. Refer to complete directions accompanying set.

2.3 Dosage as a Substitute for Oral Nicardipine Therapy

The intravenous infusion rate required to produce an average plasma concentration equivalent to a given oral dose at steady state is shown in the following table:

2.4 Dosage for Initiation of Therapy in a Drug-Free Patient

The time course of blood pressure decrease is dependent on the initial rate of infusion and the frequency of dosage adjustment. Nicardipine hydrochloride injection is administered by slow continuous infusion at a concentration of 0.1 mg/mL. With constant infusion, blood pressure begins to fall within minutes. It reaches about 50% of its ultimate decrease in about 45 minutes.

When treating acute hypertensive episodes in patients with chronic hypertension, discontinuation of infusion is followed by a 50% offset of action in 30 minutes ± 7 minutes but plasma levels of drug and gradually decreasing antihypertensive effects exist for many hours.

Titration

For a gradual reduction in blood pressure, initiate therapy at a rate of 5 mg/hr. If desired blood pressure reduction is not achieved at this dose, increase the infusion rate by 2.5 mg/hr every 15 minutes up to a maximum of 15 mg/hr, until desired blood pressure reduction is achieved. For more rapid blood pressure reduction, titrate every 5 minutes.

Maintenance

Adjust the rate of infusion as needed to maintain desired response.

2.5 Conditions Requiring Infusion Adjustment

Hypotension or Tachycardia:

In case of hypotension or tachycardia, discontinue infusion. When blood pressure and heart rate stabilize, restart infusion at low doses such as 30 mL/hr to 50 mL/hr (3 mg/hr to 5 mg/hr) and titrate to maintain desired blood pressure.

Infusion Site Changes:

Change infusion site every 12 hours if administered via peripheral vein.

Impaired Cardiac, Hepatic, or Renal Function:

Monitor closely when titrating nicardipine hydrochloride injection in patients with congestive heart failure or impaired hepatic or renal function [see Warnings and Precautions (5-5.4, 5-5.5 and 5-5.6)].

2.6 Transfer to Oral Antihypertensive Agents

If treatment includes transfer to an oral antihypertensive agent other than nicardipine capsules, initiate oral therapy upon discontinuation of nicardipine hydrochloride injection.

When switching to a TID regimen of nicardipine capsules, administer the first dose 1 hour prior to discontinuation of the infusion.

3 DOSAGE FORMS & STRENGTHS

Nicardipine hydrochloride is available in the following presentations:

25 mg nicardipine hydrochloride in 10 mL injection (2.5 mg/mL) in a single dose vial
20 mg nicardipine hydrochloride in 200 mL 0.9% sodium chloride injection (0.1 mg/mL) in a flexible container
40 mg nicardipine hydrochloride in 200 mL 0.9% sodium chloride injection (0.2 mg/mL) in a flexible container

4 CONTRAINDICATIONS

4.1 Advanced Aortic Stenosis

Do not use nicardipine in patients with advanced aortic stenosis because of the afterload reduction effect of nicardipine. Reduction of diastolic pressure in these patients may worsen rather than improve myocardial oxygen balance.

5 WARNINGS AND PRECAUTIONS

5.1 Excessive Pharmacologic Effects

In administrating nicardipine, close monitoring of blood pressure and heart rate is required. Nicardipine may occasionally produce symptomatic hypotension or tachycardia. Avoid systemic hypotension when administering the drug to patients who have sustained an acute cerebral infarction or hemorrhage.

5.2 Rapid Decreases in Blood Pressure

No clinical events have been reported suggestive of a too rapid decrease in blood pressure with nicardipine. However, as with any antihypertensive agent, blood pressure lowering should be accomplished over as long a time as is compatible with the patient's clinical status.

5.3 Use in Patients with Angina

Increases in frequency, duration, or severity of angina have been seen in chronic oral therapy with nicardipine capsules. Induction or exacerbation of angina has been seen in less than 1% of coronary artery disease patients treated with nicardipine. The mechanism of this effect has not been established.

5.4 Use in Patients with Congestive Heart Failure

Nicardipine reduced afterload without impairing myocardial contractility in preliminary hemodynamic studies of CHF patients. However, in vitro and in some patients, a negative inotropic effect has been observed. Therefore, monitor vital signs carefully when using nicardipine, particularly in combination with a beta-blocker, in patients with CHF or significant left ventricular dysfunction.

5.5 Use in Patients with Impaired Hepatic Function

Since nicardipine is metabolized in the liver, consider lower dosages and closely monitor response. Nicardipine administered intravenously increased hepatic venous pressure gradient by 4 mmHg in cirrhotic patients at high doses (5 mg/20 min) in one study. Use caution in patients with portal hypertension.

5.6 Use in Patients with Impaired Renal Function

When nicardipine was given to mild-to-moderate hypertensive patients with moderate renal impairment, a significantly lower systemic clearance and higher AUC was observed. These results are consistent with those seen after oral administration of nicardipine. Careful dose titration is advised when treating patients with more than mild renal impairment.

5.7 Intravenous Infusion Site

To reduce the possibility of venous thrombosis, phlebitis, local irritation, swelling, extravasation, and the rare occurrence of vascular impairment, administer drug through large peripheral veins or central veins rather than arteries or small peripheral veins, such as those on the dorsum of the hand or wrist. To minimize the risk of peripheral venous irritation, consider changing the site of the drug infusion every 12 hours.

5.8 Beta-Blocker Withdrawal

Nicardipine is not a beta-blocker and therefore gives no protection against the dangers of abrupt beta-blocker withdrawal. Withdraw beta-blockers gradually.

5.9 Use in Patients with Pheochromocytoma

Only limited clinical experience exists in use of nicardipine for patients with hypertension from pheochromocytoma.

6 ADVERSE REACTIONS

6.1 Adverse Reactions Observed in Clinical Trials

Because clinical trials are conducted under widely varying conditions, adverse reaction rates observed in the clinical trials of a drug cannot be directly compared to rates in the clinical trials of another drug and may not reflect the rates observed in practice.

Two hundred forty-four patients participated in two multicenter, double-blind, placebo-controlled trials of nicardipine. Adverse experiences were generally not serious and most were expected consequences of vasodilation. Adverse reactions occasionally required dosage adjustment. Therapy was discontinued in approximately 12% of patients, mainly due to hypotension, headache, and tachycardia. Adverse reactions that occurred more often on nicardipine than on placebo by at least 2% were headache (13%) and nausea/vomiting (4%).

The following adverse reactions have been reported in clinical trials or in the literature during the use of intravenously administered nicardipine.

Body as a Whole: fever, neck pain
Cardiovascular: angina pectoris, atrioventricular block, ST segment depression, inverted T wave, deep-vein thrombophlebitis
Digestive: dyspepsia
Hemic and Lymphatic: thrombocytopenia
Metabolic and Nutritional: hypophosphatemia, peripheral edema
Nervous: confusion, hypertonia
Respiratory: respiratory disorder
Special Senses: conjunctivitis, ear disorder, tinnitus
Urogenital: urinary frequency

Sinus node dysfunction and myocardial infarction, which may be due to disease progression, have been seen in patients on chronic therapy with orally administered nicardipine.

7 DRUG INTERACTIONS

7.1 Antihypertensive Agents

Since nicardipine hydrochloride injection may be administered to patients already being treated with other medications, including other antihypertensive agents, careful monitoring of these patients is necessary to detect and to treat promptly any undesired effects from concomitant administration.

7.2 Beta-Blockers

In most patients, nicardipine hydrochloride injection can safely be used concomitantly with beta-blockers. However, monitor response carefully when combining nicardipine hydrochloride injection with a beta-blocker in the treatment of congestive heart failure patients [see Warnings and Precautions (5-5.4)].

7.3 Cimetidine

Cimetidine has been shown to increase nicardipine plasma concentrations with oral nicardipine administration. Carefully monitor patients receiving the two drugs concomitantly. Data with other histamine-2 antagonists are not available.

7.4 Digoxin

Studies have shown that oral nicardipine usually does not alter digoxin plasma concentrations.

7.5 Cyclosporine

Concomitant administration of oral or intravenous nicardipine and cyclosporine results in elevated plasma cyclosporine levels through nicardipine inhibition of hepatic microsomal enzymes, including CYP3A4. Monitor closely plasma concentrations of cyclosporine during nicardipine hydrochloride injection administration, and adjust the dose of cyclosporine accordingly.

7.6 Tacrolimus

Concomitant administration of intravenous nicardipine and tacrolimus may result in elevated plasma tacrolimus levels through nicardipine inhibition of hepatic microsomal enzymes, including CYP3A4. Closely monitor plasma concentrations of tacrolimus during nicardipine administration, and adjust the dose of tacrolimus accordingly.

7.7 In Vitro Interaction

The plasma protein binding of nicardipine was not altered when therapeutic concentrations of furosemide, propranolol, dipyridamole, warfarin, quinidine, or naproxen were added to human plasma in vitro.

8 USE IN SPECIFIC POPULATIONS

8.1 Pregnancy

Pregnancy Category C.

There are no adequate and well-controlled studies of nicardipine use in pregnant women. There are limited human data in pregnant women with pre-eclampsia and preterm labor. In animal reproduction and developmental toxicity studies, evidence of fetal harm was observed. Therefore use nicardipine during pregnancy only if the potential benefit justifies the potential risk to the fetus.

In reproduction studies conducted in rats and rabbits, increased embryolethality occurred when nicardipine was administered intravenously at doses equivalent to human intravenous doses of 1.6 (rats) and 0.32 mg/kg/day (rabbits).

Increased embryolethality was also observed when nicardipine was administered orally to pregnant rabbits at a dose equivalent to a human oral dose of about 48 mg/kg/day (a dose 24 times the maximum recommended human oral dose and one associated with marked maternal body weight gain suppression). At a lower oral dose, equivalent to a human dose of about 32 mg/kg/day (16 times the maximum recommended human oral dose), in a different strain of rabbit, there were no adverse effects on the fetus, though there was increased maternal mortality. There was no evidence of embyolethality or teratogenicity when pregnant rats were administered nicardipine orally at a dose equivalent to a human oral dose of about 16 mg/kg/day (8 times the MRHD); however, dystocia, reduced birth weight, reduced neonatal survival and reduced neonatal weight gain were reported [see Nonclinical Toxicology (13.3)].

8.3 Nursing Mothers

Nicardipine is minimally excreted into human milk. Among 18 infants exposed to nicardipine through breast milk in the postpartum period, calculated daily infant dose was less than 0.3 mcg and there were no adverse events observed. It is recommended that women who wish to breastfeed should not be given this drug.

In a study of 11 women who received oral nicardipine 4 days to 14 days postpartum, 4 women received immediate-release nicardipine 40 to 80 mg daily, 6 women received sustained-release nicardipine 100 mg to 150 mg daily, and one woman received intravenous nicardipine 120 mg daily. The peak milk concentration was 7.3 mcg/L (range 1.9 to 18.8), and the mean milk concentration was 4.4 mcg/L (range 1.3 to 13.8).

Infants received an average of 0.073% of the weight-adjusted maternal oral dose and 0.14% of the weight-adjusted maternal intravenous dose.

In another study of seven women who received intravenous nicardipine for an average of 1.9 days in the immediate postpartum period as therapy for pre-eclampsia, 34 milk samples were obtained at unspecified times and nicardipine was undetectable (less than 5 mcg/L) in 82% of the samples. Four women who received 1 to 6.5 mg/hour of nicardipine had 6 milk samples with detectable nicardipine levels (range 5.1 to 18.5 mcg/L). The highest concentration of 18.5 mcg/L was found in a woman who received 5.5 mg/hour of nicardipine. The estimated maximum dose in a breastfed infant was less than 0.3 mcg daily or 0.015% to 0.004% of the therapeutic dose in a 1 kg infant.

8.4 Pediatric Use

Safety and efficacy in patients under the age of 18 have not been established.

8.5 Geriatric Use

The steady-state pharmacokinetics of nicardipine are similar in elderly hypertensive patients (greater than 65 years) and young healthy adults.

Clinical studies of nicardipine did not include sufficient numbers of subjects aged 65 and over to determine whether they respond differently from younger subjects.

Other reported clinical experience has not identified differences in responses between the elderly and younger patients. In general, dose selection for an elderly patient should be cautious, usually starting at the low end of the dosing range, reflecting the greater frequency of decreased hepatic, renal or cardiac function, and concomitant disease of other drug therapy.

10 OVERDOSAGE

Several overdosages with orally administered nicardipine have been reported. One adult patient allegedly ingested 600 mg of nicardipine immediate release capsules, and another patient, 2160 mg of the sustained release formulation of nicardipine. Symptoms included marked hypotension, bradycardia, palpitations, flushing, drowsiness, confusion and slurred speech. All symptoms resolved without sequelae. An overdosage occurred in a one-year-old child who ingested half of the powder in a 30 mg nicardipine standard capsule. The child remained asymptomatic.

Based on results obtained in laboratory animals, lethal overdose may cause systemic hypotension, bradycardia (following initial tachycardia) and progressive atrioventricular conduction block. Reversible hepatic function abnormalities and sporadic focal hepatic necrosis were noted in some animal species receiving very large doses of nicardipine.

For treatment of overdosage, standard measures including monitoring of cardiac and respiratory functions should be implemented. The patient should be positioned to avoid cerebral anoxia. Frequent blood pressure determinations are essential. Vasopressors are clinically indicated for patients exhibiting profound hypotension. Intravenous calcium gluconate may help reverse the effects of calcium entry blockade.

11 DESCRIPTION

Nicardipine hydrochloride is a calcium ion influx inhibitor (slow channel blocker or calcium channel blocker). Nicardipine hydrochloride for intravenous administration contains 2.5 mg/mL of nicardipine hydrochloride. Nicardipine hydrochloride is a dihydropyridine derivative with IUPAC (International Union of Pure and Applied Chemistry) chemical name (±)-2-(benzyl-methyl amino) ethyl methyl 1,4-dihydro-2, 6-dimethyl-4- (m-nitrophenyl)-3,5-pyridinedicarboxylate monohydrochloride and has the following structure:

Nicardipine hydrochloride is a yellow to pale yellow, odorless, crystalline powder that has a melting point range of 165-170◦ C. It is soluble in methanol, sparingly soluble in ethanol, slightly soluble in acetone, chloroform and water. It has a molecular weight of 515.99.

Nicardipine hydrochloride injection is available as a sterile, non-pyrogenic, clear, yellow solution in 10 mL vials for intravenous infusion after dilution. Each mL contains 2.5 mg nicardipine hydrochloride, 0.305 mg benzoic acid, USP and 7.5 mg sodium chloride, USP, in Water for Injection, USP. Sodium hydroxide, NF, may have been added to adjust pH to 3.5.

Nicardipine Hydrochloride in 0.9% Sodium Chloride Injection is available as a single-use, ready-to-use, iso-osmotic, clear, yellow solution for intravenous administration in a 200 mL flexible container. Each mL contains 0.1 mg or 0.2 mg nicardipine hydrochloride in 9 mg Sodium Chloride, USP. Hydrochloric acid may have been added to adjust pH.

12 CLINICAL PHARMACOLOGY

12.1 Mechanism of Action

Nicardipine inhibits the transmembrane influx of calcium ions into cardiac muscle and smooth muscle without changing serum calcium concentrations. The contractile processes of cardiac muscle and vascular smooth muscle are dependent upon the movement of extracellular calcium ions into these cells through specific ion channels. The effects of nicardipine are more selective to vascular smooth muscle than cardiac muscle. In animal models, nicardipine produced relaxation of coronary vascular smooth muscle at drug levels which cause little or no negative inotropic effect.

12.2 Pharmacodynamics

Hemodynamics

Nicardipine produces significant decreases in systemic vascular resistance. In a study of intra-arterially administered nicardipine, the degree of vasodilation and the resultant decrease in blood pressure were more prominent in hypertensive patients than in normotensive volunteers. Administration of nicardipine to normotensive volunteers at dosages of 0.25 to 3 mg/hr for eight hours produced changes of less than 5 mmHg in systolic blood pressure and less than 3 mmHg in diastolic blood pressure.

An increase in heart rate is a normal response to vasodilation and decrease in blood pressure; in some patients these increases in heart rate may be pronounced. In placebo-controlled trials, the mean increases in heart rate were 7 ± 1 bpm in postoperative patients and 8 ± 1 bpm in patients with severe hypertension at the end of the maintenance period.

Hemodynamic studies following intravenous dosing in patients with coronary artery disease and normal or moderately abnormal left ventricular function have shown significant increases in ejection fraction and cardiac output with no significant change, or a small decrease, in left ventricular end-diastolic pressure (LVEDP). There is evidence that nicardipine increases blood flow. Coronary dilatation induced by nicardipine improves perfusion and aerobic metabolism in areas with chronic ischemia, resulting in reduced lactate production and augmented oxygen consumption. In patients with coronary artery disease, nicardipine, administered after beta-blockade, significantly improved systolic and diastolic left ventricular function.

In congestive heart failure patients with impaired left ventricular function, nicardipine increased cardiac output both at rest and during exercise. Decreases in left ventricular end-diastolic pressure were also observed. However, in some patients with severe left ventricular dysfunction, it may have a negative inotropic effect and could lead to worsened failure.

“Coronary steal” has not been observed during treatment with nicardipine (Coronary steal is the detrimental redistribution of coronary blood flow in patients with coronary artery disease from underperfused areas toward better perfused areas.) Nicardipine has been shown to improve systolic shortening in both normal and hypokinetic segments of myocardial muscle. Radionuclide angiography has confirmed that wall motion remained improved during increased oxygen demand. (Occasional patients have developed increased angina upon receiving nicardipine capsules. Whether this represents coronary steal in these patients, or is the result of increased heart rate and decreased diastolic pressure, is not clear.)

In patients with coronary artery disease, nicardipine improves left ventricular diastolic distensibility during the early filling phase, probably due to a faster rate of myocardial relaxation in previously underperfused areas. There is little or no effect on normal myocardium, suggesting the improvement is mainly by indirect mechanisms such as afterload reduction and reduced ischemia. Nicardipine has no negative effect on myocardial relaxation at therapeutic doses. The clinical benefits of these properties have not yet been demonstrated.

Electrophysiologic Effects

In general, no detrimental effects on the cardiac conduction system have been seen with nicardipine. During acute electrophysiologic studies, it increased heart rate and prolonged the corrected QT interval to a minor degree. It did not affect sinus node recovery or SA conduction times. The PA, AH, and HV intervals* or the functional and effective refractory periods of the atrium were not prolonged. The relative and effective refractory periods of the His-Purkinje system were slightly shortened.

*PA = conduction time from high to low right atrium; AH = conduction time from low right atrium to His bundle deflection, or AV nodal conduction time; HV = conduction time through the His bundle and the bundle branch-Purkinje system.

Hepatic Function

Because nicardipine is extensively metabolized by the liver, plasma concentrations are influenced by changes in hepatic function. In a clinical study with nicardipine capsules in patients with severe liver disease, plasma concentrations were elevated and the half-life was prolonged [see Warnings and Precautions (5.5)]. Similar results were obtained in patients with hepatic disease when nicardipine hydrochloride was administered for 24 hours at 0.6 mg/hr.

Renal Function

When nicardipine was given to mild-to-moderate hypertensive patients with moderate degrees of renal impairment, significant reduction in glomerular filtration rate (GFR) and effective renal plasma flow (RPF) were observed. No significant differences in liver blood flow were observed in these patients. A significantly lower systemic clearance and higher area under the curve (AUC) were observed.

When nicardipine capsules (20 or 30 mg TID) were given to hypertensive patients with impaired renal function, mean plasma concentrations, AUC, and Cmax were approximately two-fold higher than in healthy controls. There was a transient increase in electrolyte excretion, including sodium [see Warnings and Precautions (5.6)].

Acute bolus administration of nicardipine hydrochloride injection (2.5 mg) in healthy volunteers decreased mean arterial pressure and renal vascular resistance; glomerular filtration rate (GFR), renal plasma flow (RPF), and the filtration fraction were unchanged. In healthy patients undergoing abdominal surgery, nicardipine hydrochloride injection (10 mg over 20 minutes) increased GFR with no change in RPF when compared with placebo. In hypertensive type ll diabetic patients with nephropathy, nicardipine capsules (20 mg TID) did not change RPF and GFR, but reduced renal vascular resistance.

Pulmonary Function

In two well-controlled studies of patients with obstructive airway disease treated with nicardipine capsules, no evidence of increased bronchospasm was seen. In one of the studies, nicardipine capsules improved forced expiratory volume 1 second (FEV1) and forced vital capacity (FVC) in comparison with metoprolol. Adverse reactions reported in a limited number of patients with asthma, reactive airway disease, or obstructive airway disease were similar to reactions in other patients treated with nicardipine capsules.

12.3 Pharmacokinetics

Distribution

A rapid dose-related increase in nicardipine plasma concentrations is seen during the first two hours after the start of an infusion of nicardipine. Plasma concentrations increase at a much slower rate after the first few hours, and approach steady state at 24 to 48 hours. The steady-state pharmacokinetics of nicardipine are similar in elderly hypertensive patients (greater than 65 years) and young healthy adults. On termination of the infusion, nicardipine concentrations decrease rapidly, with at least a 50% decrease during the first two hours post-infusion. The effects of nicardipine on blood pressure significantly correlate with plasma concentrations. Nicardipine is highly protein bound (greater than 95%) in human plasma over a wide concentration range.

Following infusion, nicardipine plasma concentrations decline triexponentially, with a rapid early distribution phase (α-half-life of 3 minutes), an intermediate phase (ß-half-life of 45 minutes), and a slow terminal phase (ƴ-half-life of 14 hours) that can only be detected after long-term infusions. Total plasma clearance (Cl) is 0.4 L/hr•kg, and the apparent volume of distribution (Vd) using a non-compartment model is 8.3 L/kg. The pharmacokinetics of nicardipine is linear over the dosage range of 0.5 mg/hr to 40 mg/hr.

Metabolism and Excretion

Nicardipine has been shown to be rapidly and extensively metabolized by the hepatic cytochrome P450 enzymes, CYP2C8, 2D6, and 3A4. Nicardipine does not induce or inhibit its own metabolism; however, nicardipine has been shown to inhibit certain cytochrome P450 enzymes (including CYP3A4, CYP2D6, CYP2C8, and CYP2C19). Inhibition of these enzymes may result in increased plasma levels of certain drugs, including cyclosporine and tacrolimus [see Drug Interactions (7.5, 7.6)]. The altered pharmacokinetics may necessitate dosage adjustment of the affected drug or discontinuation of treatment.

After coadministration of a radioactive intravenous dose of nicardipine with an oral 30 mg dose given every 8 hours, 49% of the radioactivity was recovered in the urine and 43% in the feces within 96 hours. None of the dose was recovered as unchanged nicardipine.

13 NONCLINICAL TOXICOLOGY

13.1 Carcinogenesis, Mutagenesis, Impairment of Fertility

Rats treated with nicardipine in the diet (at concentrations calculated to provide daily dosage levels of 5, 15, or 45 mg/kg/day) for two years showed a dose-dependent increase in thyroid hyperplasia and neoplasia (follicular adenoma/carcinoma). One-month and three-month studies in the rat have suggested that these results are linked to a nicardipine-induced reduction in plasma thyroxine (T4) levels with a consequent increase in plasma levels of thyroid stimulating hormone (TSH). Chronic elevation of TSH is known to cause hyperstimulation of the thyroid.

In rats on an iodine deficient diet, nicardipine administration for one month was associated with thyroid hyperplasia that was prevented by T4 supplementation. Mice treated with nicardipine in the diet (at concentrations calculated to provide daily dosage levels of up to 100 mg/kg/day) for up to 18 months showed no evidence of neoplasia of any tissue and no evidence of thyroid changes.

There was no evidence of thyroid pathology in dogs treated with up to 25 mg nicardipine/kg/day for one year and no evidence of effects of nicardipine on thyroid function (plasma T4 and TSH) in man.

There was no evidence of a mutagenic potential of nicardipine in a battery of genotoxicity tests conducted on microbial indicator organisms, in micronucleus tests in mice and hamsters, or in a sister chromatid exchange study in hamsters.

No impairment of fertility was seen in male or female rats administered nicardipine at oral doses as high as 100 mg/kg/day (human equivalent dose about 16 mg/kg/day, 8 times the maximum recommended human oral dose).

13.3 Reproductive and Developmental Toxicology

Embryolethality, but no teratogenicity, was seen at intravenous doses of 10 mg nicardipine/kg/day in rats and 1 mg/kg/day in rabbits. These doses in the rat and rabbit are equivalent to human intravenous doses of about 1.6 and 0.32 mg/kg/day, respectively. (The total daily human dose delivered by a continuous intravenous infusion ranges from 1.2 to 6 mg/kg/day, depending on duration at different infusion rates ranging from 3 to 15 mg/hr as individual patients are titrated for optimal results.) Nicardipine was also embryocidal when administered orally to pregnant Japanese White rabbits, during organogenesis, at 150 mg/kg/day (a dose associated with marked body weight gain suppression in the treated doe), but not at 50 mg/kg/day (human equivalent dose about 16 mg/kg/day or about 8 times the maximum recommended human oral dose). No adverse effects on the fetus were observed when New Zealand albino rabbits were treated orally, during organogenesis, with up to 100 mg/kg/day (a dose associated with significant mortality in the treated doe). In pregnant rats administered nicardipine orally at doses of up to 100 mg/kg/day (human equivalent dose about 16 mg/kg/day) there was no evidence of embryolethality or teratogenicity. However, dystocia, reduced birth weight, reduced neonatal survival and reduced neonatal weight gain were noted.

14 CLINICAL STUDIES

Effects in Hypertension

In patients with mild-to-moderate chronic stable essential hypertension, nicardipine hydrochloride injection (0.5 to 4 mg/hr) produced dose-dependent decreases in blood pressure, although only the decreases at 4 mg/hr were statistically different from placebo. At the end of a 48-hour infusion at 4 mg/hr, the decreases were 26 mmHg (17%) in systolic blood pressure and 21 mmHg (20%) in diastolic blood pressure. In other settings (e.g., patients with severe or postoperative hypertension), nicardipine hydrochloride injection (5 to 15 mg/hr) produced dose-dependent decreases in blood pressure. Higher infusion rates produced therapeutic responses more rapidly. The mean time to therapeutic response for severe hypertension, defined as diastolic blood pressure less than or equal to 95 mmHg or greater or equal to 25 mmHg decrease and systolic blood pressure less than or equal to 160 mmHg, was 77 ± 5 minutes. The average maintenance dose was 8.0 mg/hr. The mean time to therapeutic response for postoperative hypertension, defined as greater than or equal to 15% reduction in diastolic or systolic blood pressure, was 12 minutes. The average maintenance dose was 3 mg/hr.

16 HOW SUPPLIED/STORAGE AND HANDLING

NICARDIPINE HYDROCHLORIDE INJECTION is supplied in the following dosage forms.
NDC 51662-1482-1
NICARDIPINE HYDROCHLORIDE INJECTION 25mg/10mL (2.5 mg/mL) 10mL VIAL

HF Acquisition Co LLC, DBA HealthFirst
Mukilteo, WA 98275

Also supplied in the following manufacture supplied dosage forms

16.1 How Supplied

Nicardipine Hydrochloride Injection is available in packages as follows:

Nicardipine Hydrochloride in 0.9% Sodium Chloride Injection is available in packages as follows:

16.2 Storage and Handling

Store at 20° to 25°C (68° to 77°F) [See USP Controlled Room Temperature].

Freezing does not adversely affect the product, but exposure to elevated temperatures should be avoided. Protect from light. Store vials in carton until used.

SPL UNCLASSIFIED

Manufactured by:
HIKMA FARMACÊUTICA (PORTUGAL), S.A.
Estrada do Rio da Mó, 8, 8A e 8B - Fervença - 2705-906 Terrugem SNT, PORTUGAL

Manufactured by:
EXELA PHARMA SCIENCES, LLC.
1245 Blowing Rock Blvd.
Lenoir, NC 28645

Distributed by:
WEST-WARD PHARMACEUTICALS CORP.
Eatontown, NJ 07724

Revised September 2016